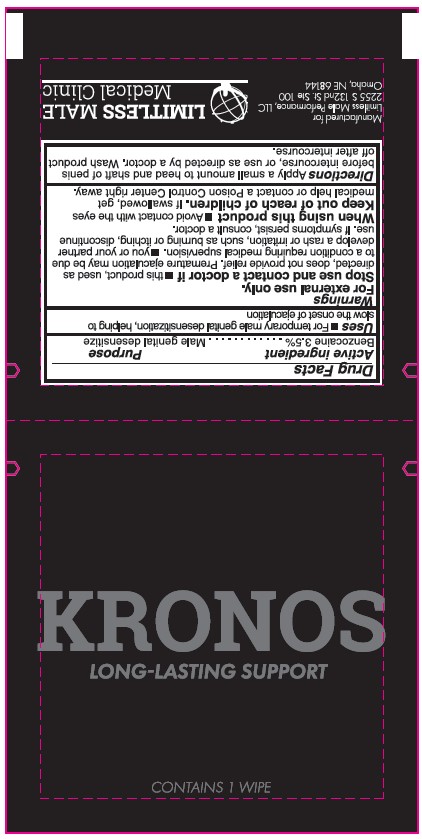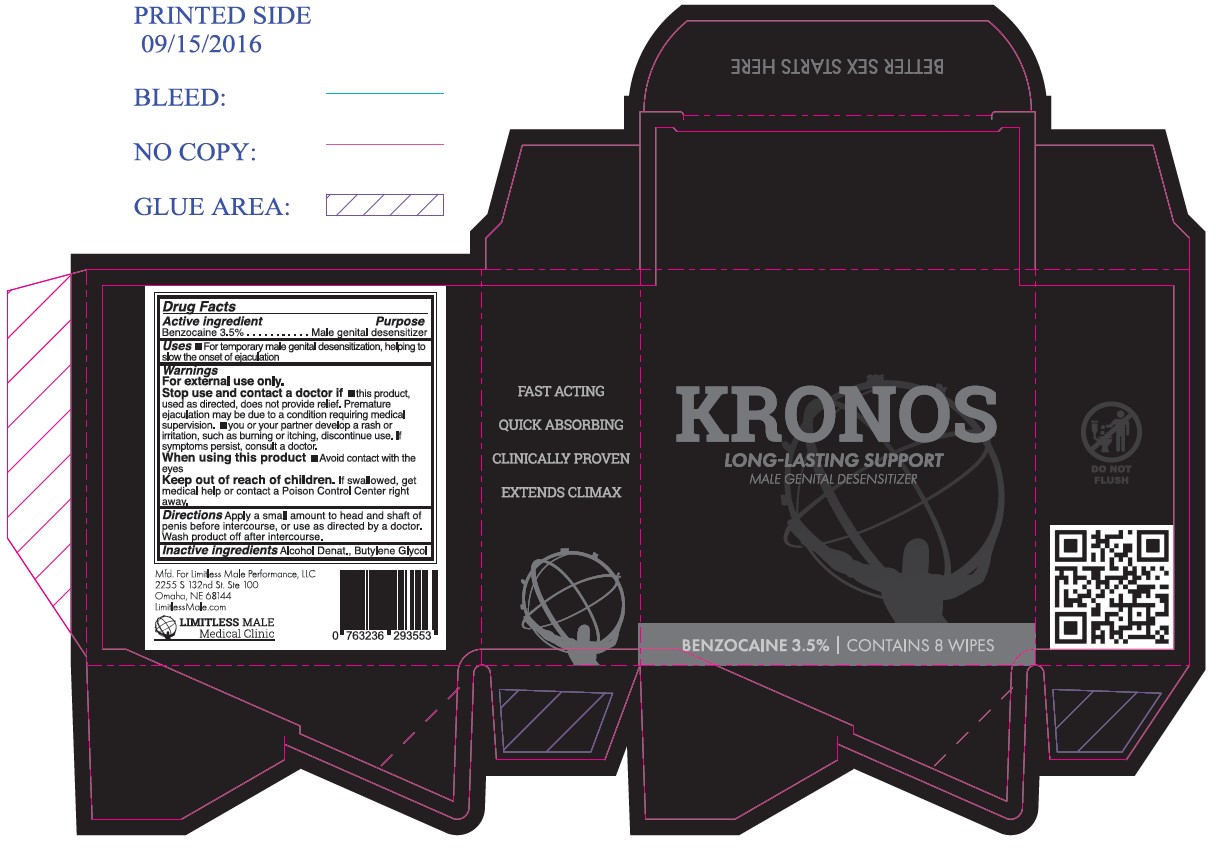 DRUG LABEL: Men Delay Wipe
NDC: 82659-1000 | Form: CLOTH
Manufacturer: Limitless Male Medical Clinic
Category: otc | Type: HUMAN OTC DRUG LABEL
Date: 20231211

ACTIVE INGREDIENTS: BENZOCAINE 3.5 g/100 g
INACTIVE INGREDIENTS: BUTYLENE GLYCOL; ALCOHOL

KRONOS
LONG-LASTING SUPPORT

Active Ingredient

Benzocaine 3.5%

Purpose

Male genital desensitizer

Uses

For temporary male genital desensitization, helping to slow the onset of ejaculation

Warnings

For external use only.

Stop use and contact a doctor if

- this product , used as directed, does not provide relief. Premature ejaculation may be due to a condition requiring medical supervision.
- you or your partner develop a rash or irritation, such as burning or itching, discontinue use. If symptoms persist, consult a doctor.

When using this product

Avoid contact with the eyes

Keep out of reach of children.

If swallowed, get medical help or contact a Poison Control Center right away

Directions

Apply a small amount to head and shaft of penis before intercourse, or use as directed by a doctor.

Wash product off after intercourse.

Inactive Ingredients

Alcohol Denat., Butylene Glycol

Label

KRONOS

LONG-LASTING SUPPORT

CONTAINS 1 WIPE

Manufactured for

Limitless Male Performance, LLC

2255 S 132nd St. Ste 100

Omaha, NE 68144

LIMITLESS MALE

Medical Clinic

KRONOS

LONG-LASTING SUPPORT

MALE GENITAL DESENSITIZER

BENZOCAINE 3.5% I CONTAINS 8 WIPES

FAST ACTING

QUICK ABSORBING

CLINICALLY PROVEN

EXTENDS CLIMAX

Mfd. for Limitless Male Performance, LLC

2255 S 132nd St. Ste 100

Omaha, NE 68144

LIMITLESS MALE

Medical Clinic

0 763236 293553